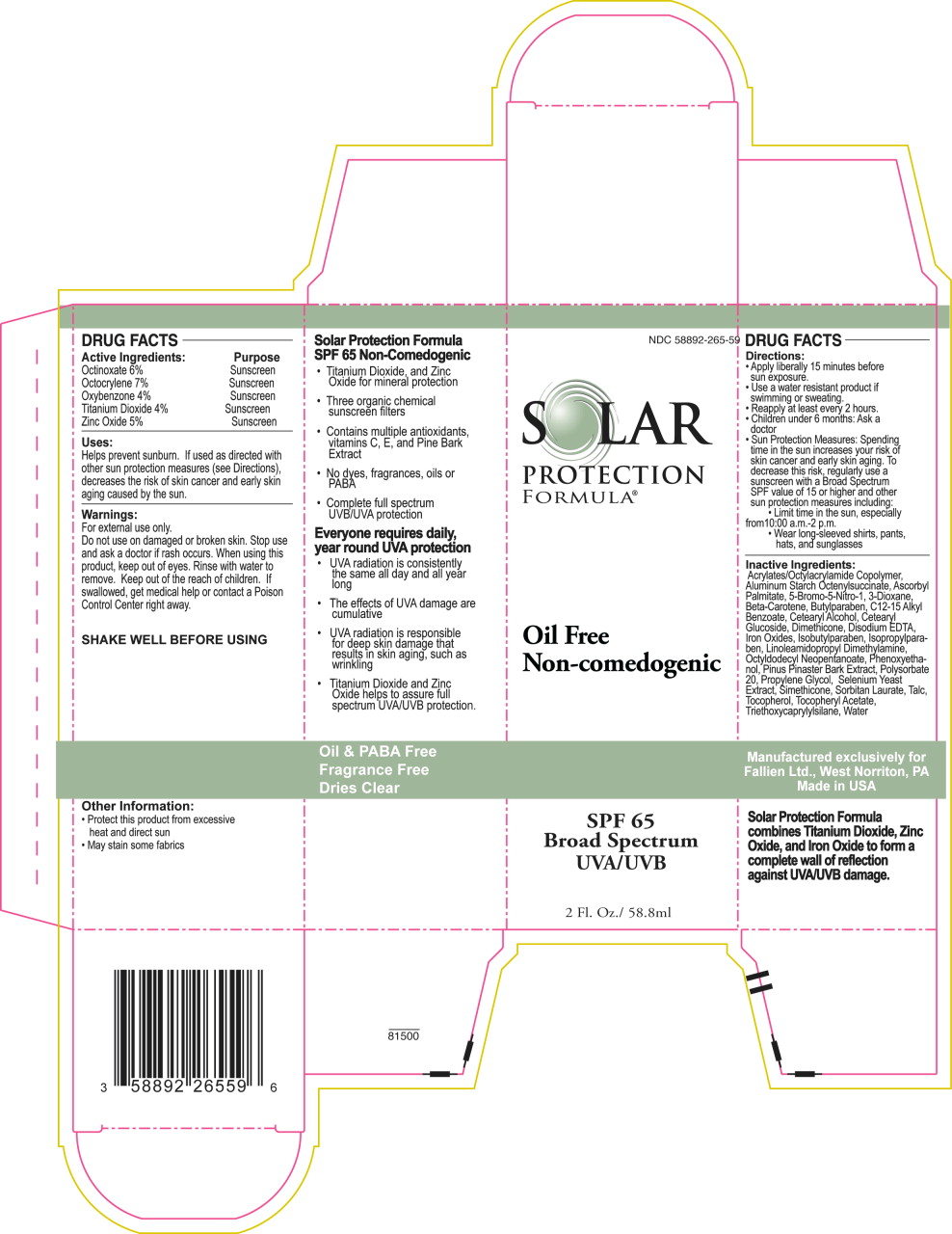 DRUG LABEL: Solar Protection Formula SPF 65 
NDC: 58892-265 | Form: LOTION
Manufacturer: Fallien Cosmeceuticals, LTD.
Category: otc | Type: HUMAN OTC DRUG LABEL
Date: 20121227

ACTIVE INGREDIENTS: Octinoxate 60 mg/1 mL; Octocrylene 70 mg/1 mL; Oxybenzone 40 mg/1 mL; Titanium Dioxide 40 mg/1 mL; Zinc Oxide 50 mg/1 mL
INACTIVE INGREDIENTS: Alkyl (C12-15) Benzoate; Aluminum Starch Octenylsuccinate; Ascorbyl Palmitate; 5-Bromo-5-Nitro-1,3-Dioxane; .Beta.-Carotene; Butylparaben; Cetostearyl Alcohol; Cetearyl Glucoside; Dimethicone; Edetate Disodium; Ferric Oxide Red; Isobutylparaben; Isopropylparaben; Linoleamidopropyl Dimethylamine; Octyldodecyl Neopentanoate; Phenoxyethanol; Maritime Pine; Polysorbate 20; Propylene Glycol; Sorbitan Monolaurate; Talc; Tocopherol; .Alpha.-Tocopherol Acetate; Triethoxycaprylylsilane; Water

DRUG FACTS

Active Ingredients:

Octinoxate 6%

Octocrylene 7%

Oxybenzone 4%

Titanium Dioxide 4%

Zinc Oxide 5%

Purpose

Sunscreen

Sunscreen

Sunscreen

Sunscreen

Sunscreen

Uses:

Helps prevent sunburn. If used as directed with other sun protection measures (see Directions), decreases the risk of skin cancer and early skin aging caused by the sun.

Warnings:

For external use only.

Do not use on damaged or broken skin.

Stop use and ask a doctor if rash occurs.

When using this product, keep out of eyes. Rinse with water to remove.

KEEP OUT OF REACH OF CHILDREN

Keep out of the reach of children. If swallowed, get medical help or contact a Poison Control Center right away.

SHAKE WELL BEFORE USING

Other Information:

- Protect this product from excessive heat and direct sun
- May stain some fabrics

Directions:

- Apply liberally 15 minutes before sun exposure.
- Use a water resistant product if swimming or sweating.
- Reapply at least every 2 hours.
- Children under 6 months: Ask a doctor
- Sun Protection Measures: Spending time in the sun increases your risk of skin cancer and early skin aging. To decrease this risk, regularly use a sunscreen with a Broad Spectrum SPF value of 15 or higher and other sun protection measures including:
  - Limit time in the sun, especially from 10:00 a.m.-2 p.m.
  - Wear long-sleeved shirts, pants, hats, and sunglasses

Inactive Ingredients:

Acrylates/Octylacrylamide Copolymer, Aluminum Starch Octenylsuccinate, Ascorbyl Palmitate, 5-Bromo-5-Nitro-1, 3-Dioxane, Beta-Carotene, Butylparaben, C12-15 Alkyl Benzoate, Cetearyl Alcohol, Cetearyl Glucoside, Dimethicone, Disodium EDTA, Iron Oxides, Isobutylparaben, Isopropylparaben, Linoleamidopropyl Dimethylamine, Octyldodecyl Neopentanoate, Phenoxyethanol, Pinus Pinaster Bark Extract, Polysorbate 20, Propylene Glycol, Selenium Yeast Extract, Simethicone, Sorbitan Laurate, Talc, Tocopherol, Tocopheryl Acetate, Triethoxycaprylylsilane, Water

Solar Protection Formula combines Titanium Dioxide, Zinc Oxide, and Iron Oxide to form a complete wall of reflection against UVA/UVB damage.

Manufactured exclusively for
Fallien Ltd., West Norriton, PA
Made in USA

Principal Display Panel – 2 oz Carton Label

NDC 58892-265-59

SOLAR

PROTECTION

FORMULA®

Oil Free

Non-comedogenic

SPF 65

Broad Spectrum

UVA/UVB

2 Fl. Oz. / 58.8ml